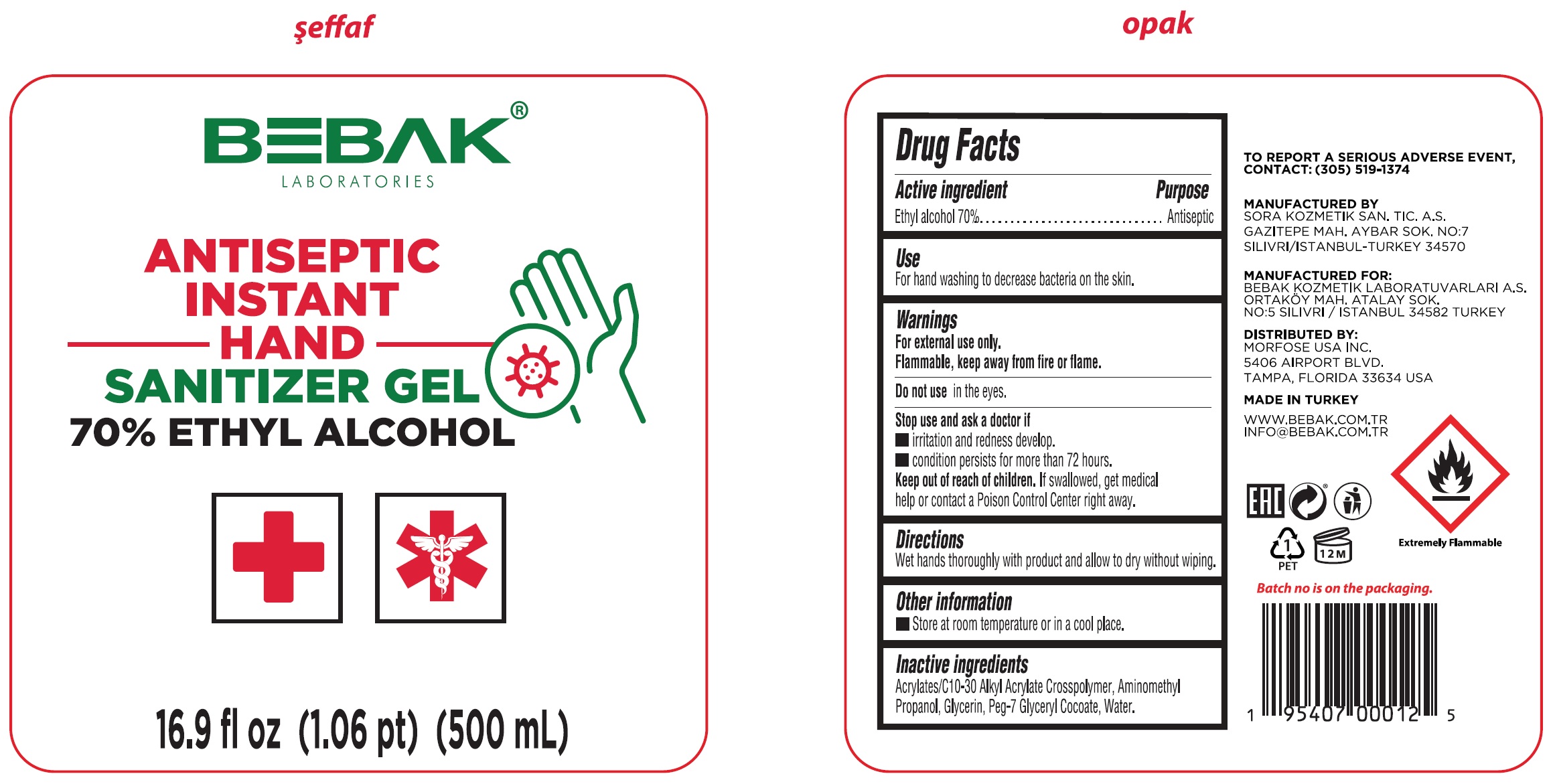 DRUG LABEL: Instant Sanitizing Gel
NDC: 77462-012 | Form: GEL
Manufacturer: SORA KOZMETIK SANAYI TICARET ANONIM SIRKETI
Category: otc | Type: HUMAN OTC DRUG LABEL
Date: 20231028

ACTIVE INGREDIENTS: ALCOHOL 0.7 mL/1 mL
INACTIVE INGREDIENTS: CARBOMER INTERPOLYMER TYPE A (ALLYL SUCROSE CROSSLINKED); AMINOMETHYLPROPANOL; GLYCERIN; PEG-7 GLYCERYL COCOATE; WATER

Instant Sanitizing Gel

Active ingredient

Ethyl alcohol 70%

Purpose

Antiseptic

Use

For hand washing to decrease bacteria on the skin.

Warnings

For external use only.

Flammable, keep away from fire or flame.

Do not use

in the eyes.

Stop use and ask a doctor if

- irritation and redness develop.
- condition persists for more than 72 hours.

Keep out of reach of children.

If swallowed, get medical help or contact a Poison Control Center right away.

Directions

Wet hands thoroughly with product and allow to dry without wiping.

Other information

- Store at room temperature or in a cool place.

Inactive ingredients

Acrylates/C10-30 Alkyl Acrylate Crosspolymer, Aminomethyl Propanol, Glycerin, Peg-7 Glyceryl Cocoate, Water.